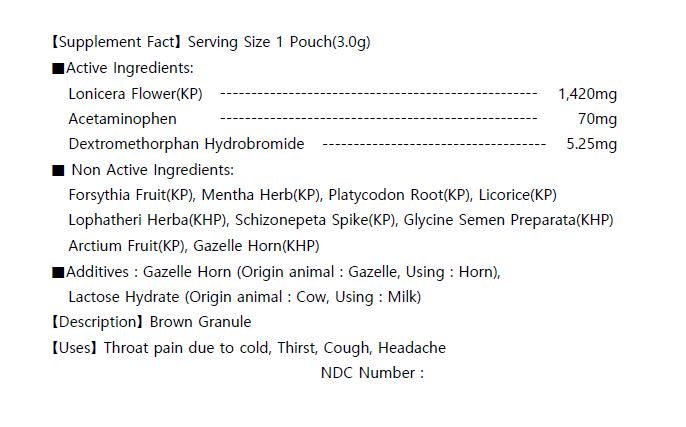 DRUG LABEL: JEGAMSAN Extract
NDC: 73442-0013 | Form: GRANULE
Manufacturer: I World Pharmaceutical Co., Ltd.
Category: otc | Type: HUMAN OTC DRUG LABEL
Date: 20200916

ACTIVE INGREDIENTS: LONICERA CAPRIFOLIUM FLOWER 1.42 g/3 g; ACETAMINOPHEN 0.07 g/3 g; DEXTROMETHORPHAN HYDROBROMIDE 0.00525 g/3 g
INACTIVE INGREDIENTS: LACTOSE MONOHYDRATE

ACTIVE INGREDIENT

Lonicera Flower(KP)
Acetaminophen
Dextromethorphan Hydrobromide

PURPOSE

throat pain due to cold, thirst, cough, headache

Keep out of reach of children

INDICATIONS AND USAGE

for adults take 1 pouch per intake, 3 times a day, before or between meals

Keep out of reach of children. In case of overdose, get medical help or contact a Poison Control Center right away.

INACTIVE INGREDIENT

Forsythia Fruit(KP), Mentha Herb(KP), Platycodon Root(KP), Lophatheri Herba(KHP), Schizonepeta Spike(KP), Glycine Semen, Arctium Fruit(KP), Gazelle Horn(KHP)

DOSAGE AND ADMINISTRATION

For oral use only